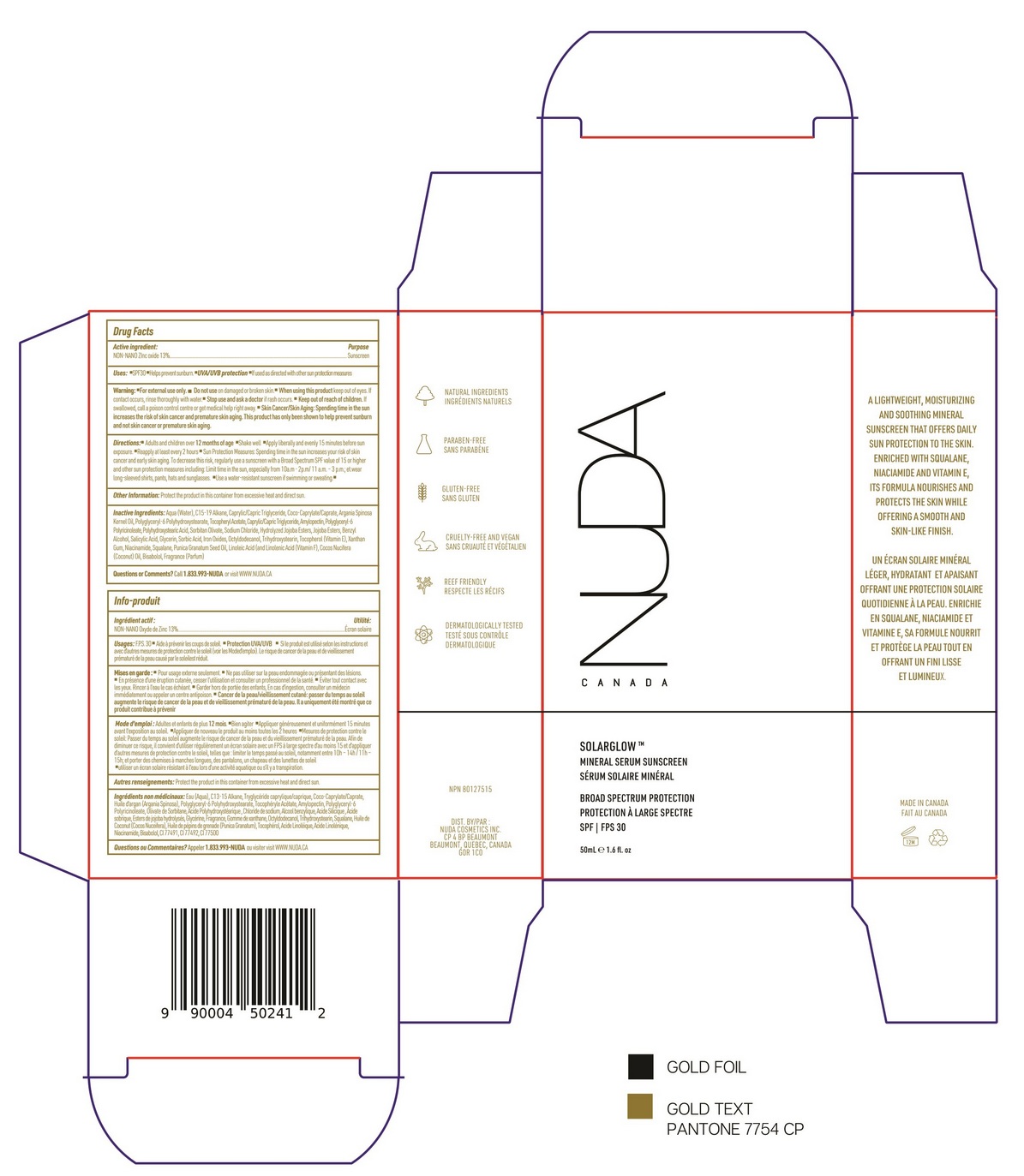 DRUG LABEL: NUDA CANADA SOLARGLOW MINERAL SERUM SUNSCREEN
NDC: 71447-058 | Form: CREAM
Manufacturer: LABORATOIRES DRUIDE INC
Category: otc | Type: HUMAN OTC DRUG LABEL
Date: 20260114

ACTIVE INGREDIENTS: ZINC OXIDE 13 g/100 mL
INACTIVE INGREDIENTS: C15-19 ALKANE; OCTYLDODECANOL; NIACINAMIDE; FRAGRANCE LAVENDER & CHIA F-153480; JOJOBA OIL; TOCOPHEROL; WATER; AMYLOPECTIN, UNSPECIFIED SOURCE; TRIHYDROXYSTEARIN; PUNICA GRANATUM SEED OIL; LINOLEIC ACID; POLYHYDROXYSTEARIC ACID STEARATE; ARGANIA SPINOSA SEED; BENZYL ALCOHOL; HYDROLYZED JOJOBA ESTERS (ACID FORM); SORBITAN OLIVATE; SQUALANE; CAPRYLIC/CAPRIC/LINOLEIC TRIGLYCERIDE; SODIUM CHLORIDE; COCO-CAPRYLATE; GLYCERIN; XANTHAN GUM; POLYGLYCERYL-6 POLYRICINOLEATE; POLYGLYCERYL-6 STEARATE; SALICYLIC ACID; SORBIC ACID; BROWN IRON OXIDE; LEVOMENOL; COCOS NUCIFERA WHOLE

NUDA CANADA SOLARGLOW MINERAL SERUM SUNSCREEN SPF30 50mL

Active Ingredients

Zinc Oxide 13%

Purpose

Sunscreen

Uses

▪ Helps prevent sunburn. ▪ If used as directed with other sun protection measures (see Directions), decreases the risk of skin cancer and early skin aging caused by the sun.

Warnings

For external use only

Do not use

on damaged or broken skin.

Stop use and ask a doctor if

rash occurs.

Keep out of reach of children

If swallowed, get medical help or contact Poison Control Center right away.

Directions

▪ Apply liberally and evenly 15 minutes before sun exposure ▪ Reapply ▪ After 80 minutes of swimming or sweating ▪ Immediately after towel drying ▪ At least every 2 hours ▪ Sun Protection Measures▪ Spending time in the sun increases your risk of skin cancer and early skin aging. To decrease this risk, regularly use a sunscreen with a Broad Spectrum SPF value of 15 or higher and other sun protection measures including: ▪ Limit time in the sun, especially from 10 a.m. - 2 p.m. ▪ Wear long-sleeved shirts, pants, hats, and sunglasses ▪ Use a water-resistant sunscreen if swimming or sweating.

Other Information

Protect the product in this container from excessive heat and direct sun.

Inactive Ingredients

Aqua (Water), C15-19 Alkane, Caprylic/Capric Triglyceride, Coco-Caprylate/Caprate, Argania Spinosa Kernel Oil, Polyglyceryl-6 Polyhydroxystearate, Tocopheryl Acetate, Caprytic/Capric Triglyceride, Amylopectin, Polyglyceryl-6 Polyricinoleate, Polyhydroxystearic Acid, Sorbitan Olivate, Sodium Chloride, Hydrolyzed Jojoba Esters, Jojoba Esters, Benzyl Alcohol, Salicylic Acid, Glycerin, Sorbic Acid, Iron Oxides, Octyldodecanol, Trihydroxystearin, Tocopherol (Vitamin E), Xanthan Gum, Niacinamide, Squalane, Punica Granatum Seed Oil, Linoleic Acid (and Linolenic Acid (Vitamin F), Cocos Nucifera (Coconut) Oil, Bisabolol, Fragrance (Parfum).

Questions or Comments?

Call 1.833.993-NUDA
or visit www.nuda.ca